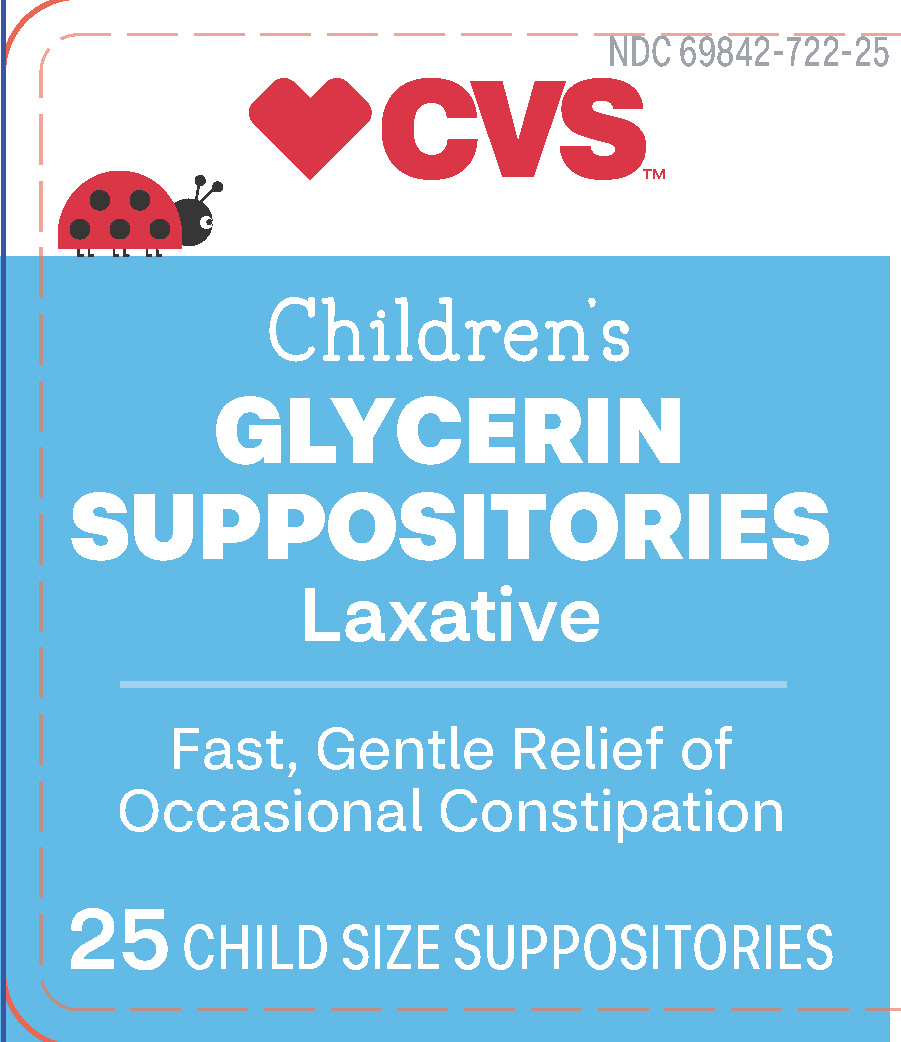 DRUG LABEL: Glycerin								
NDC: 69842-722 | Form: SUPPOSITORY
Manufacturer: CVS Pharmacy
Category: otc | Type: HUMAN OTC DRUG LABEL
Date: 20251024

ACTIVE INGREDIENTS: GLYCERIN 1 g/1.2 1
INACTIVE INGREDIENTS: SODIUM HYDROXIDE; STEARIC ACID; WATER

CVS Pediatric Glycerin Supp

Active ingredient (in each suppository)

Glycerin 1g

Purpose

Laxative

Uses

- for relief of occasional constipation
- this product generally produces a bowel movement in 1/4 to 1 hour

Warnings

For rectal use only

May cause rectal discomfort or a burning sensation

Ask a Doctor before using any laxative if child has

- abdominal pain, nausea or vomiting
- a sudden change in bowel habits lasting more than two weeks
- already used a laxative for more than 1 week

Stop use and consult a doctor if child has

- rectal bleeding
- no bowel movement within 1 hour of using this product

These symptoms may indicate a serious condition.

Keep out of reach of children.

If swallowed, get medical help or contact a Poison Control Center right away.

Directions

Single daily dosage

childrien 2 to under 6 1 suppository, or as directed by a doctor

children under 2 years ask a doctor

Insert suppository well up into rectum.

Suppository need not melt completely to produce laxative action.

Other information

- Store container tightly closed.
- Keep away from excessive heat.

Inactive ingredients

purified water, sodium hydroxide, stearic acid

Pediatric Glycerin Suppositories, 25 count

CVS_Ped 25ct.jpg

Pediatric Glycerin Suppositories 25 count, CVS